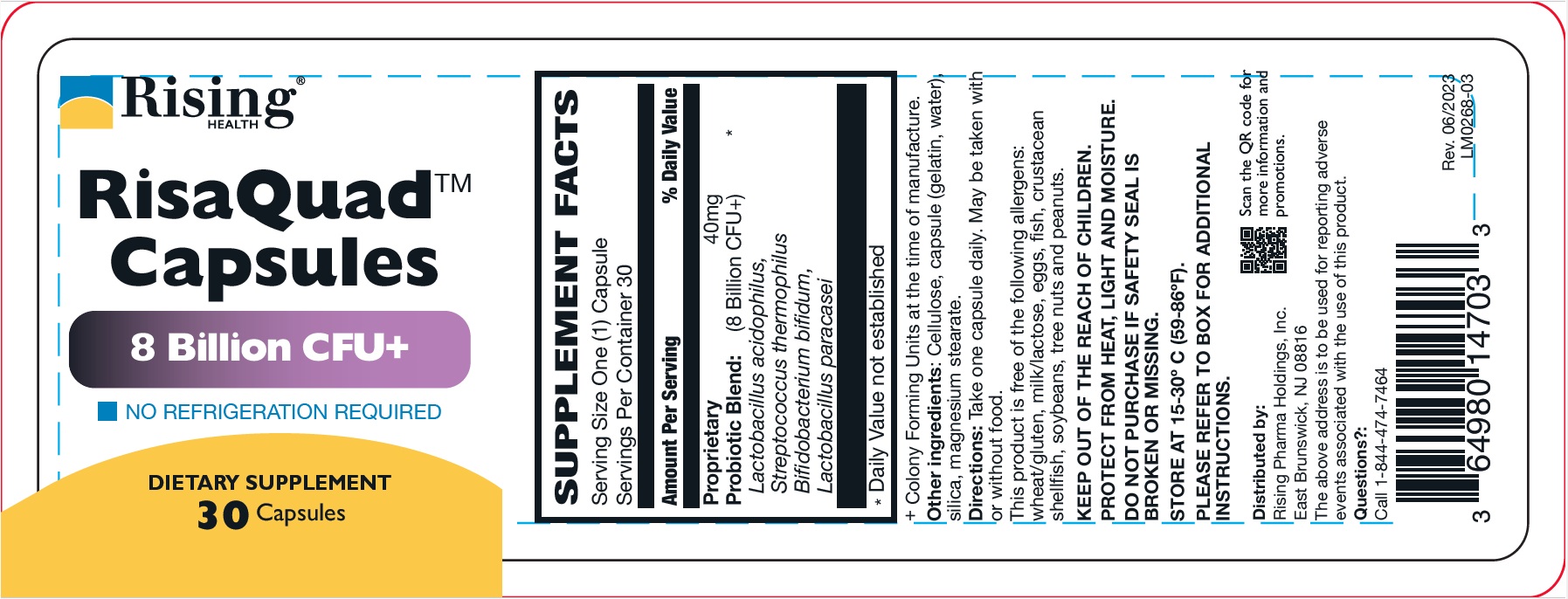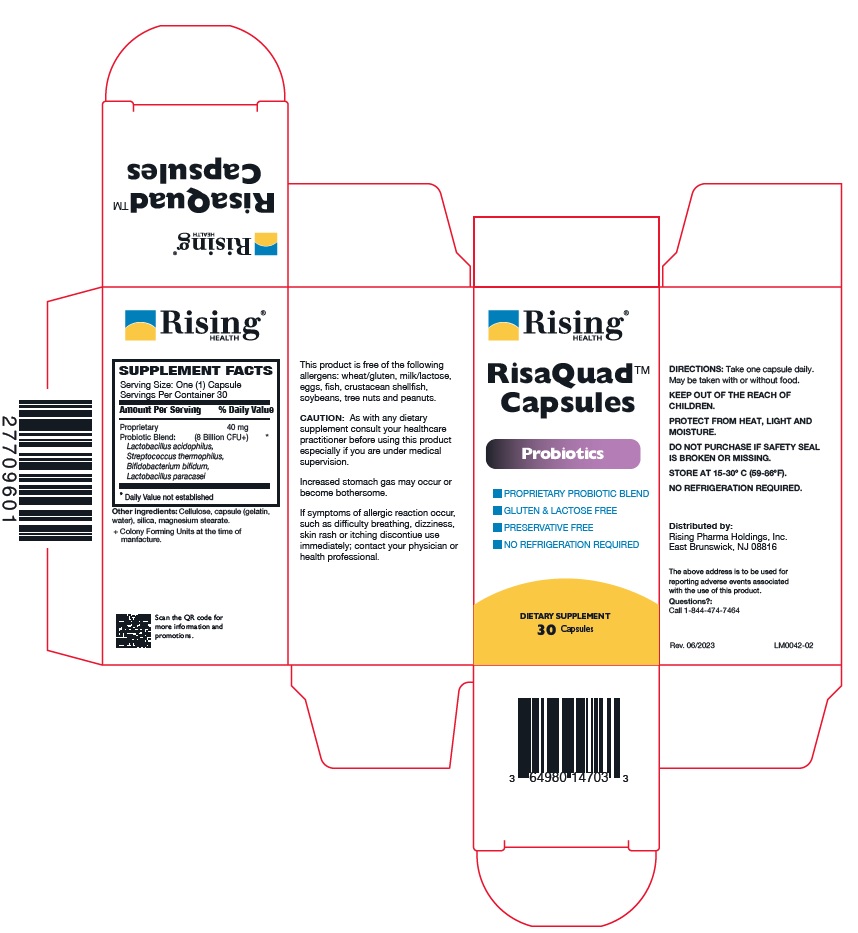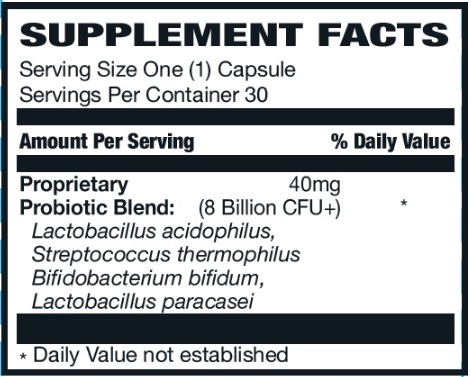 DRUG LABEL: RisaQuad
NDC: 64980-147 | Form: CAPSULE
Manufacturer: Rising Pharma Holdings, Inc.
Category: other | Type: DIETARY SUPPLEMENT
Date: 20250806

ACTIVE INGREDIENTS: LACTOBACILLUS ACIDOPHILUS 8000000000 [CFU]/1 1; BIFIDOBACTERIUM 8000000000 [CFU]/1 1; LACTICASEIBACILLUS PARACASEI 8000000000 [CFU]/1 1; STREPTOCOCCUS THERMOPHILUS 8000000000 [CFU]/1 1
INACTIVE INGREDIENTS: MICROCRYSTALLINE CELLULOSE; GELATIN; WATER; MAGNESIUM STEARATE; SILICON DIOXIDE

RisaQuadTM Capsules, Dietary Supplement, 30 Capsules

HEALTH CLAIM

Other ingredients: Cellulose, capsule (gelatin, water), silica, magnesium stearate.

+Colony Forming Units at the time of manufacture.

This product is free of the following allergens: wheat/gluten, milk/lactose, eggs, fish, crustacean shellfish, soybeans, tree nuts and peanuts.

WARNINGS

CAUTION: As with any dietary supplement consult your healthcare practitioner before using this product especially if you are under medical supervision.

Increased stomach gas may occur or become bothersome.

If symptoms of allergic reaction occur, such as difficulty breathing, dizziness, skin rash or itching discontiue use immediately; contact your physician or health professional.

DOSAGE AND ADMINISTRATION

DIRECTIONS: Take one capsule daily. May be taken with or without food.

SAFE HANDLING WARNING

KEEP OUT OF THE REACH OF CHILDREN.

PROTECT FROM HEAT, LIGHT AND MOISTURE.

DO NOT PURCHASE IF SAFETY SEAL IS BROKEN OR MISSING.

STORE AT 15-30º C (59-86ºF).

NO REFRIGERATION REQUIRED.

Distributed by:

Rising Pharma Holdings, Inc.
East Brunswick, NJ 08816

The above address is to be used for reporting adverse events associated with the use of this product.

Questions?:Call 1-844-474-7464

Rev. 06/2023

PACKAGE LABEL.PRINCIPAL DISPLAY PANEL

RisaQuadTM Capsules

DIETARY SUPPLEMENT

30 Capsules

Bottle Label (64980-147-03)

Carton Label (64980-147-03)